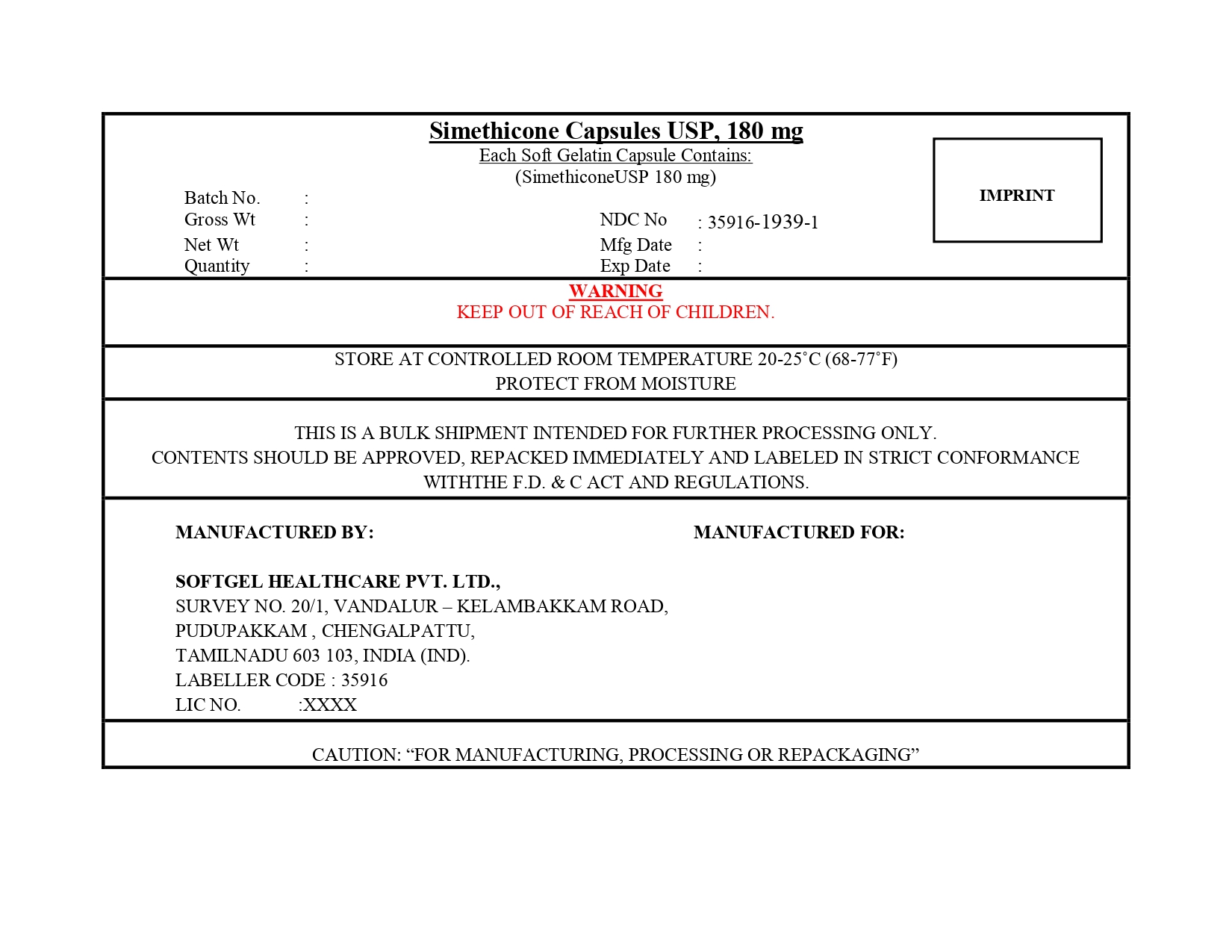 DRUG LABEL: Simethicone
NDC: 35916-1939 | Form: CAPSULE, LIQUID FILLED
Manufacturer: SOFTGEL HEALTHCARE PRIVATE LIMITED
Category: otc | Type: HUMAN OTC DRUG LABEL
Date: 20260128

ACTIVE INGREDIENTS: DIMETHICONE 180 mg/1 1
INACTIVE INGREDIENTS: SORBITOL; TITANIUM DIOXIDE; WATER; FD&C YELLOW NO. 6; PEPPERMINT OIL; GELATIN; GLYCERIN; SILICON DIOXIDE

Simethicone Capsules USP, 180 mg

Active ingredient (in each softgel)

Simethicone USP 180 mg

Purpose

Antigas

Use

for the relief of

- pressure, bloating, and fullness commonly referred to as gas

Warnings

Keep out of reach of children.

Directions

- adults: swallow with water 1 or 2 softgels as needed after meals and at bedtime
- do not exceed 2 softgels in 24 hours except under the advice and supervision of a physician

Other information

- store at controlled room temperature 20-25ºC (68-77ºF)
- protect from moisture
- read all product information before using.
- Keep this box for important information

Inactive ingredients

FD&C yellow no.6, gelatin, glycerin, peppermint oil, purified water, sorbitol, titanium dioxide

Principal Display Panel

NDC 35916-1939-2

Compare to Gas-X® Ultra Strength Active Ingredient*

Simethicone Capsules USP, 180 mg

Simethicone 180 mg / Antigas

RELIEVES GAS FAST:

- Pressure
- Bloating
- Discomfort

50 Softgels